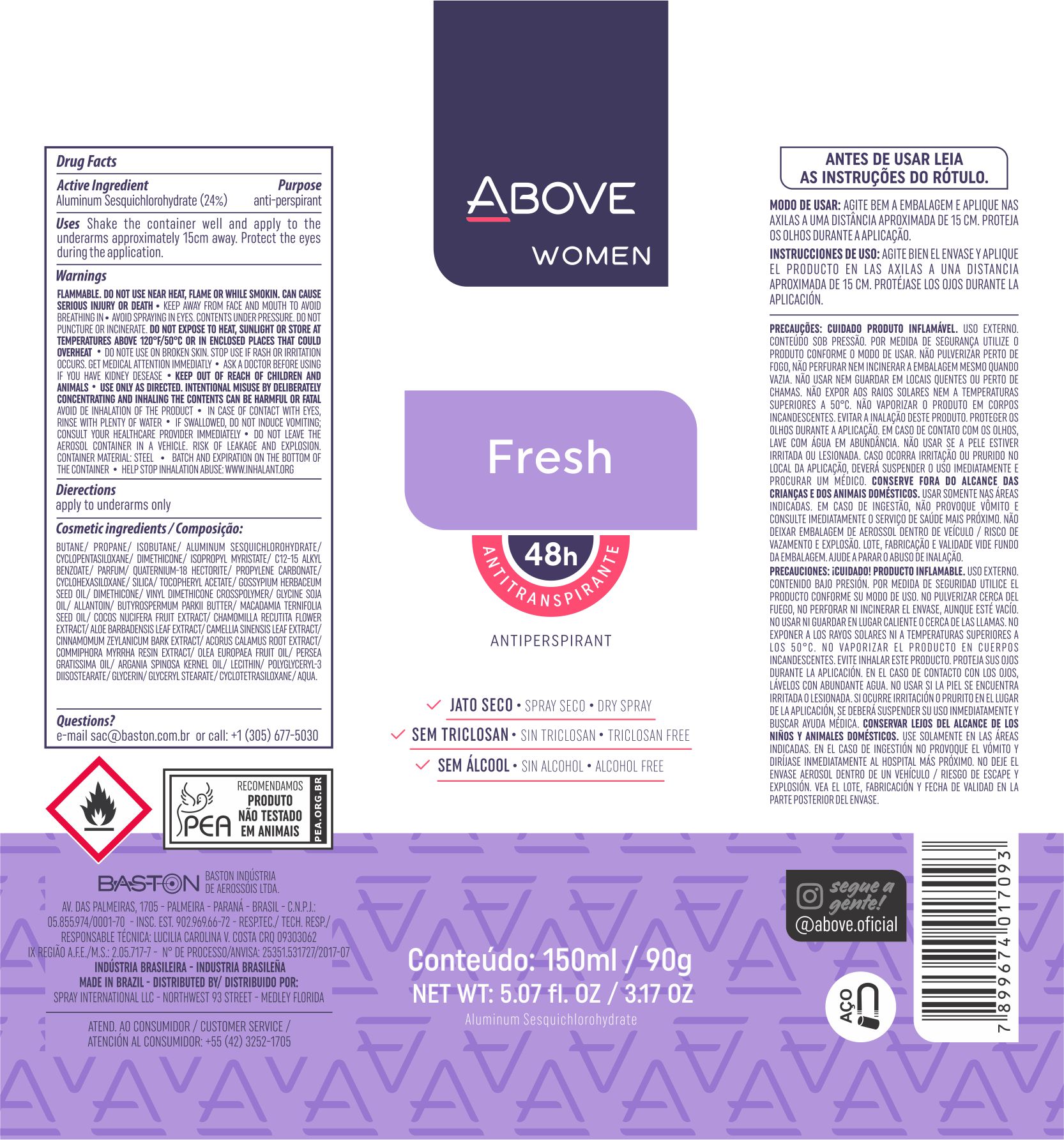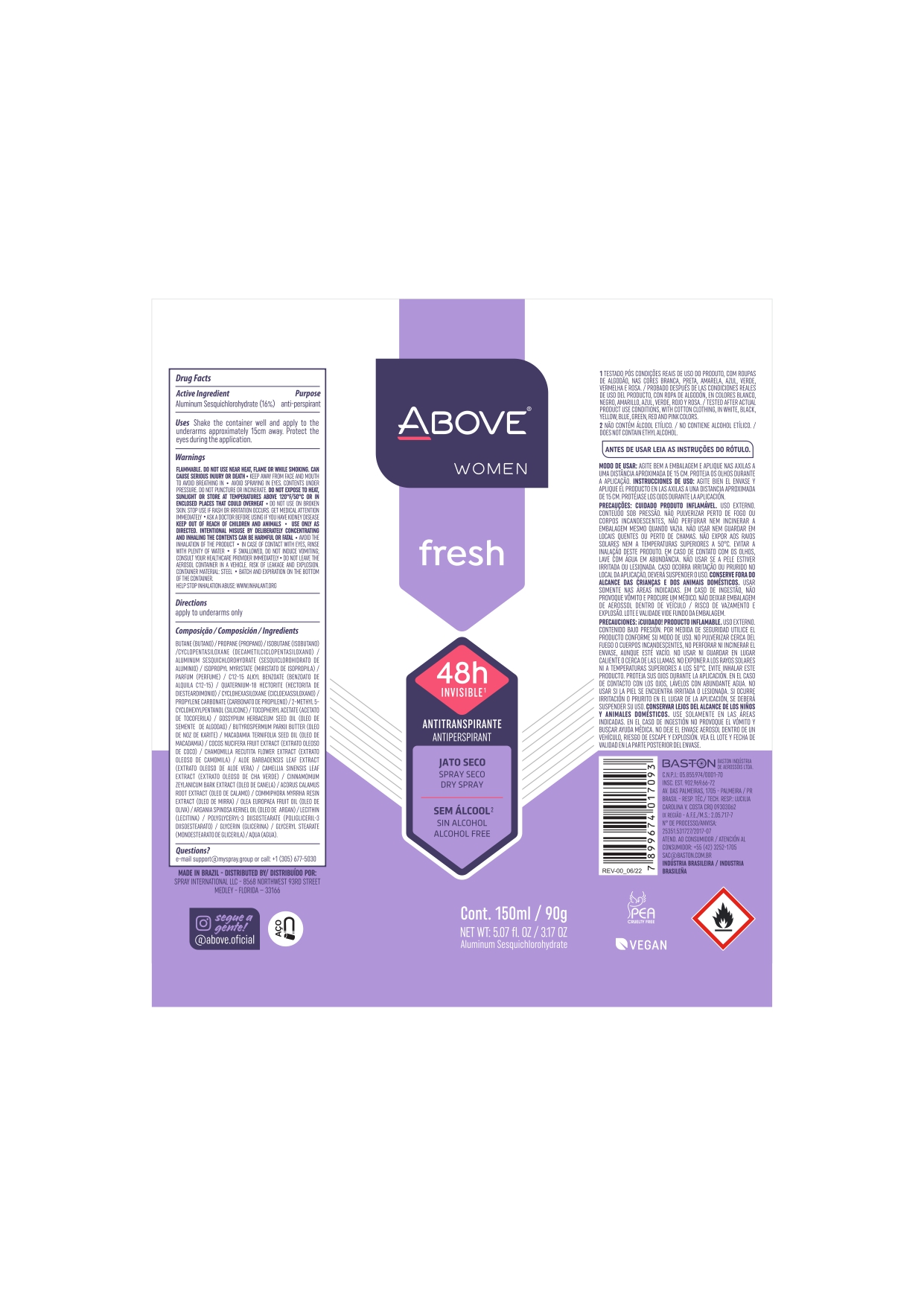 DRUG LABEL: Antiperspirant Above Fresh
NDC: 73306-1103 | Form: AEROSOL, SPRAY
Manufacturer: Baston Industria de Aerossóis Ltda
Category: otc | Type: HUMAN OTC DRUG LABEL
Date: 20241226

ACTIVE INGREDIENTS: ALUMINUM SESQUICHLOROHYDRATE 24 g/100 g
INACTIVE INGREDIENTS: GLYCERIN; POLYGLYCERYL-3 DIISOSTEARATE; COCONUT; WATER; ISOBUTANE; ARGAN OIL; .ALPHA.-TOCOPHEROL ACETATE; CINNAMON BARK OIL; MACADAMIA OIL; SHEA BUTTER; CHAMOMILE; SILICA DIMETHYL SILYLATE; ACORUS CALAMUS ROOT; BUTANE; PROPANE; LECITHIN, SOYBEAN; GREEN TEA LEAF; PROPYLENE CARBONATE; MYRRH OIL; ALLANTOIN; VINYL DIMETHICONE/METHICONE SILSESQUIOXANE CROSSPOLYMER; ALOE VERA LEAF; DIMETHICONE; LEVANT COTTON SEED; DISTEARDIMONIUM HECTORITE; GLYCERYL MONOSTEARATE; ISOPROPYL MYRISTATE; AVOCADO OIL; CYCLOMETHICONE 5

Antiperspirant Above Fresh Aerosol